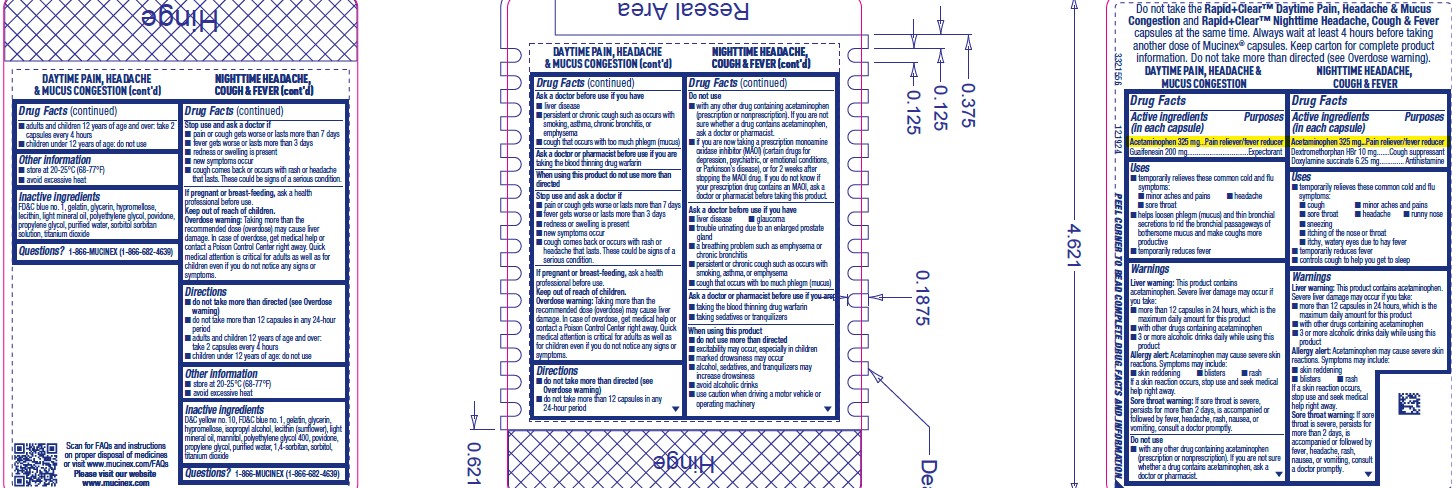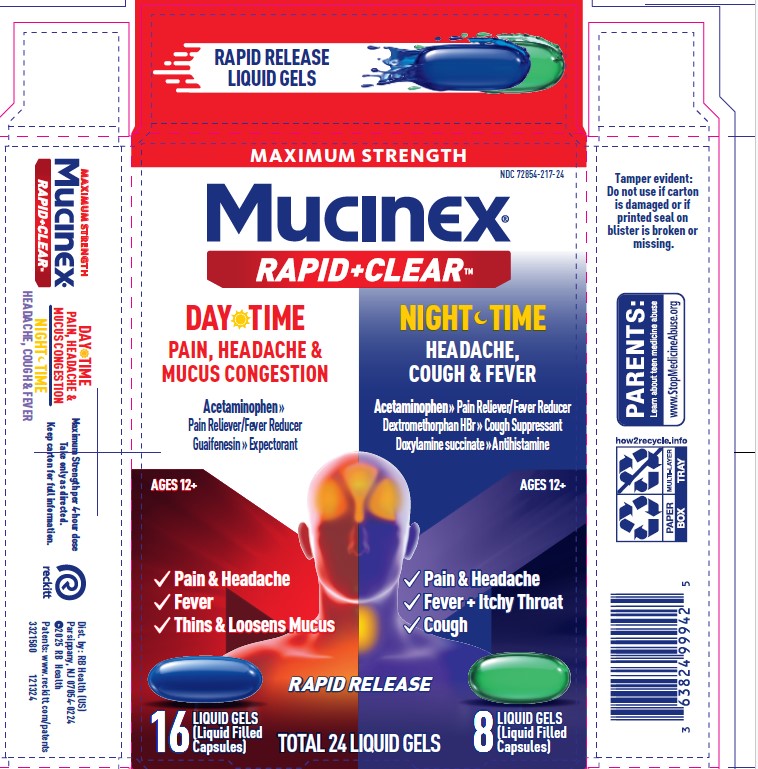 DRUG LABEL: MUCINEX Rapid Clear Pain, Headache and Mucus Congestion and Nighttime Liquid Gels
NDC: 72854-217 | Form: KIT | Route: ORAL
Manufacturer: RB Health (US) LLC
Category: otc | Type: HUMAN OTC DRUG LABEL
Date: 20251124

ACTIVE INGREDIENTS: GUAIFENESIN 200 mg/1 1; ACETAMINOPHEN 325 mg/1 1; ACETAMINOPHEN 325 mg/1 1; DEXTROMETHORPHAN HYDROBROMIDE 10 mg/1 1; DOXYLAMINE SUCCINATE 6.25 mg/1 1
INACTIVE INGREDIENTS: HYPROMELLOSES; POVIDONE; GELATIN; GLYCERIN; WATER; TITANIUM DIOXIDE; SORBITOL SOLUTION; LECITHIN, SUNFLOWER; LIGHT MINERAL OIL; PROPYLENE GLYCOL; POLYETHYLENE GLYCOL, UNSPECIFIED; FD&C BLUE NO. 1; D&C YELLOW NO. 10; FD&C BLUE NO. 1; ISOPROPYL ALCOHOL; POLYETHYLENE GLYCOL 400; 1,4-SORBITAN; LECITHIN, SUNFLOWER; WATER; SORBITOL; LIGHT MINERAL OIL; GLYCERIN; HYPROMELLOSES; PROPYLENE GLYCOL; TITANIUM DIOXIDE; GELATIN; MANNITOL; POVIDONE

MUCINEX® Rapid Clear® Pain, Headache & Mucus Congestion and Nighttime Liquid Gels

ACTIVE INGREDIENT

Day:

Acetaminophen 325 mg

Guaifenesin 200 mg

Night:

Acetaminophen 325 mg
Dextromethorphan HBr 10 mg
Doxylamine succinate 6.25 mg

PURPOSE

Day:

Acetaminophen 325 mg...Pain reliever/fever reducer
Guaifenesin 200 mg.................................Expectorant

Night:

Acetaminophen 325 mg...Pain reliever/fever reducer
Dextromethorphan HBr 10 mg.......Cough suppressant
Doxylamine succinate 6.25 mg............. Antihistamine

INDICATIONS AND USAGE

Day:

Uses
■ temporarily relieves these common cold and flu
symptoms:
■ minor aches and pains ■ headache
■ sore throat
■ helps loosen phlegm (mucus) and thin bronchial
secretions to rid the bronchial passageways of
bothersome mucus and make coughs more
productive
■ temporarily reduces fever

Night:

Uses
■ temporarily relieves these common cold and flu
symptoms:
■ cough ■ minor aches and pains
■ sore throat ■ headache ■ runny nose
■ sneezing
■ itching of the nose or throat
■ itchy, watery eyes due to hay fever
■ temporarily reduces fever
■ controls cough to help you get to sleep

WARNINGS

Day:

Liver warning: This product contains
acetaminophen. Severe liver damage may occur if
you take:
■ more than 12 capsules in 24 hours, which is the
maximum daily amount for this product
■ with other drugs containing acetaminophen
■ 3 or more alcoholic drinks daily while using this
product

Allergy alert: Acetaminophen may cause severe skin
reactions. Symptoms may include:
■ skin reddening ■ blisters ■ rash
If a skin reaction occurs, stop use and seek medical
help right away.
Sore throat warning: If sore throat is severe,
persists for more than 2 days, is accompanied or
followed by fever, headache, rash, nausea, or
vomiting, consult a doctor promptly.

Do not use
■ with any other drug containing acetaminophen
(prescription or nonprescription). If you are not sure
whether a drug contains acetaminophen, ask a
doctor or pharmacist.

Ask a doctor before use if you have
■ liver disease
■ persistent or chronic cough such as occurs with
smoking, asthma, chronic bronchitis, or
emphysema
■ cough that occurs with too much phlegm (mucus)
Ask a doctor or pharmacist before use if you are
taking the blood thinning drug warfarin
When using this product do not use more than
directed

Stop use and ask a doctor if
■ pain or cough gets worse or lasts more than 7 days
■ fever gets worse or lasts more than 3 days
■ redness or swelling is present
■ new symptoms occur
■ cough comes back or occurs with rash or
headache that lasts. These could be signs of a
serious condition.

Night:

Liver warning: This product contains acetaminophen.
Severe liver damage may occur if you take:
■ more than 12 capsules in 24 hours, which is the
maximum daily amount for this product
■ with other drugs containing acetaminophen
■ 3 or more alcoholic drinks daily while using this
product

Allergy alert: Acetaminophen may cause severe skin
reactions. Symptoms may include:
■ skin reddening
■ blisters ■ rash
If a skin reaction occurs,
stop use and seek medical
help right away.

Sore throat warning: If sore
throat is severe, persists for
more than 2 days, is
accompanied or followed by
fever, headache, rash,
nausea, or vomiting, consult
a doctor promptly.

Do not use
■ with any other drug containing acetaminophen
(prescription or nonprescription). If you are not
sure whether a drug contains acetaminophen,
ask a doctor or pharmacist.
■ if you are now taking a prescription monoamine
oxidase inhibitor (MAOI) (certain drugs for
depression, psychiatric, or emotional conditions,
or Parkinson’s disease), or for 2 weeks after
stopping the MAOI drug. If you do not know if
your prescription drug contains an MAOI, ask a
doctor or pharmacist before taking this product.

Ask a doctor before use if you have
■ liver disease ■ glaucoma
■ trouble urinating due to an enlarged prostate
gland
■ a breathing problem such as emphysema or
chronic bronchitis
■ persistent or chronic cough such as occurs with
smoking, asthma, or emphysema
■ cough that occurs with too much phlegm (mucus)
Ask a doctor or pharmacist before use if you are
■ taking the blood thinning drug warfarin
■ taking sedatives or tranquilizers

When using this product
■ do not use more than directed
■ excitability may occur, especially in children
■ marked drowsiness may occur
■ alcohol, sedatives, and tranquilizers may
increase drowsiness
■ avoid alcoholic drinks
■ use caution when driving a motor vehicle or
operating machinery

Stop use and ask a doctor if
■ pain or cough gets worse or lasts more than 7 days
■ fever gets worse or lasts more than 3 days
■ redness or swelling is present
■ new symptoms occur
■ cough comes back or occurs with rash or headache
that lasts. These could be signs of a serious condition.

DOSAGE AND ADMINISTRATION

Day:

Directions
■ do not take more than directed (see
Overdose warning)
■ do not take more than 12 capsules in any
24-hour period
■ adults and children 12 years of age and over: take 2
capsules every 4 hours
■ children under 12 years of age: do not use

Night:

Directions
■ do not take more than directed (see Overdose
warning)
■ do not take more than 12 capsules in any 24-hour
period
■ adults and children 12 years of age and over:
take 2 capsules every 4 hours
■ children under 12 years of age: do not use

KEEP OUT OF REACH OF CHILDREN

If pregnant or breast-feeding, ask a health
professional before use.

Keep out of reach of children.

Overdose warning: Taking more than the
recommended dose (overdose) may cause liver
damage. In case of overdose, get medical help or
contact a Poison Control Center right away. Quick
medical attention is critical for adults as well as for
children even if you do not notice any signs or
symptoms.

Other information
■ store at 20-25°C (68-77°F)
■ avoid excessive heat

INACTIVE INGREDIENT

Day:

Inactive ingredients
FD&C blue no. 1, gelatin, glycerin, hypromellose,
lecithin, light mineral oil, polyethylene glycol, povidone,
propylene glycol, purified water, sorbitol sorbitan
solution, titanium dioxide

Night:

Inactive ingredients
D&C yellow no. 10, FD&C blue no. 1, gelatin, glycerin,
hypromellose, isopropyl alcohol, lecithin (sunflower), light
mineral oil, mannitol, polyethylene glycol 400, povidone,
propylene glycol, purified water, 1,4-sorbitan, sorbitol,
titanium dioxide

Questions? 1-866-MUCINEX (1-866-682-4639)